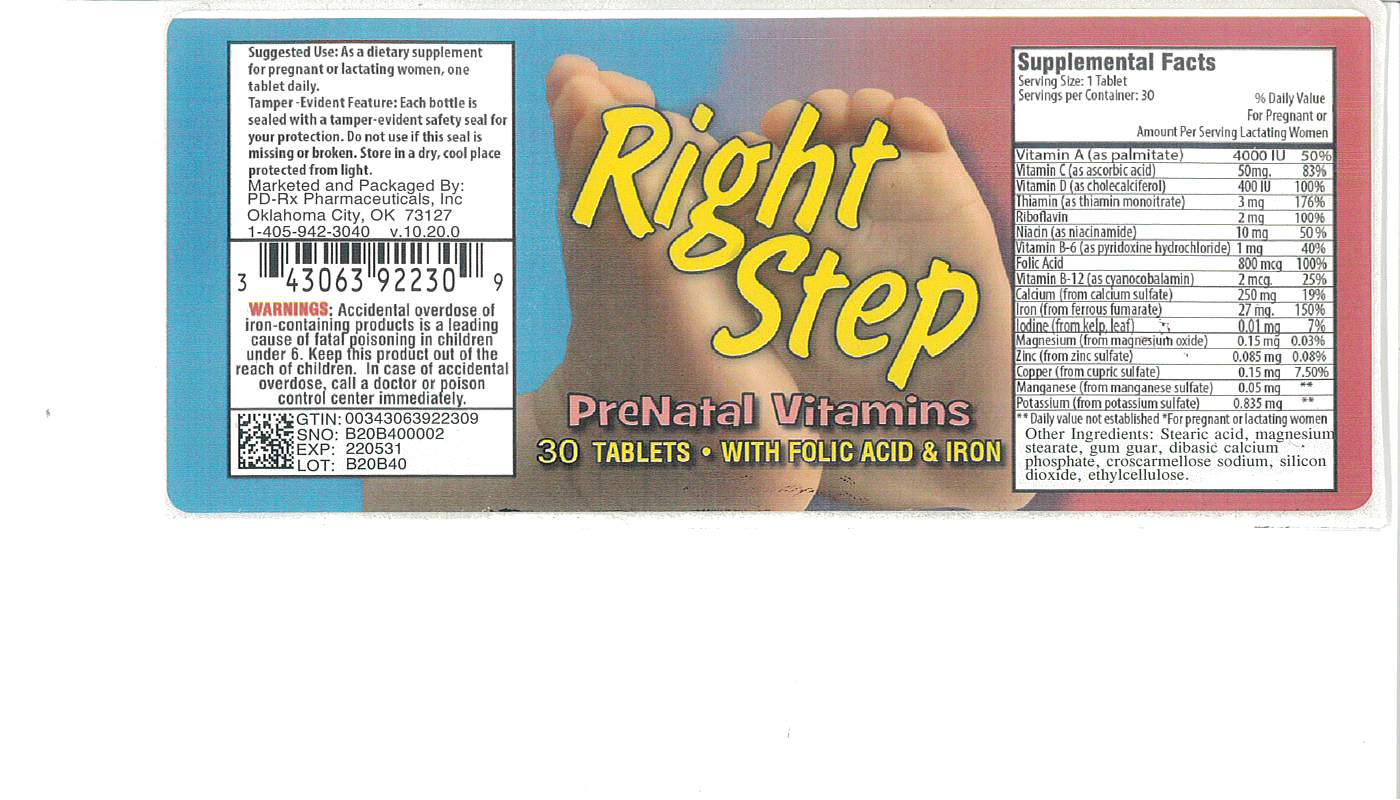 DRUG LABEL: Right Step
NDC: 43063-922 | Form: TABLET
Manufacturer: PD-Rx Pharmaceuticals, Inc.
Category: other | Type: DIETARY SUPPLEMENT
Date: 20181030

ACTIVE INGREDIENTS: VITAMIN A 4000 [iU]/1 1; ASCORBIC ACID 50 mg/1 1; VITAMIN D 400 [iU]/1 1; THIAMINE 3 mg/1 1; RIBOFLAVIN 2 mg/1 1; NIACINAMIDE 10 mg/1 1; PYRIDOXINE HYDROCHLORIDE 1 mg/1 1; FOLIC ACID 0.8 mg/1 1; CYANOCOBALAMIN 2 ug/1 1; CALCIUM SULFATE 250 mg/1 1; FERROUS FUMARATE 27 mg/1 1; LAMINARIA DIGITATA .01 mg/1 1; MAGNESIUM OXIDE 15 mg/1 1; ZINC OXIDE 0.085 mg/1 1; COPPER .15 mg/1 1; POTASSIUM SULFATE 0.835 mg/1 1
INACTIVE INGREDIENTS: CALCIUM PHOSPHATE, DIBASIC, ANHYDROUS; CROSCARMELLOSE SODIUM; SILICON DIOXIDE; STEARIC ACID; MAGNESIUM STEARATE; ETHYLCELLULOSES

SUPPLEMENT FACTS

Other Ingredients: stearic acid, magnesium stearate, gum guar, dibasic calcium phosphate, croscarmellose sodium, silicon dioxide, ethylcellulose.

Use as a dietary supplement for pregnant or lactating women.

WARNINGS

WARNING: Accidental overdose of iron-containing products is a leading cause of fatal poisoning in children under 6. KEEP THIS PRODUCT OUT OF THE REACH OF CHILDREN. In case of accidental overdose, call a doctor or poison control center immediately.

DESCRIPTION

Right Step is a tan capsule shaped tablet.

DIRECTIONS FOR USE

Take one tablet daily.

HOW SUPPLIED

Right Step is available as a tan capsule shaped tablet. Available in bottles 30 and 100.

Tamper-Evident Feature: Each bottle is sealed with a tamper-evident safety seal for your protection. Do not use if this seal is missing or broken.

STORAGE

Store in a dry, cool place protected from light.

KEEP OUT OF REACH OF CHILDREN.

PRINCIPAL DISPLAY PANEL

Right Step

Prenatal Vitamin

Marketed and Packaged by PD-Rx Pharmaceuticals, Inc. Oklahoma City, OK 73127 1-405-942-3040